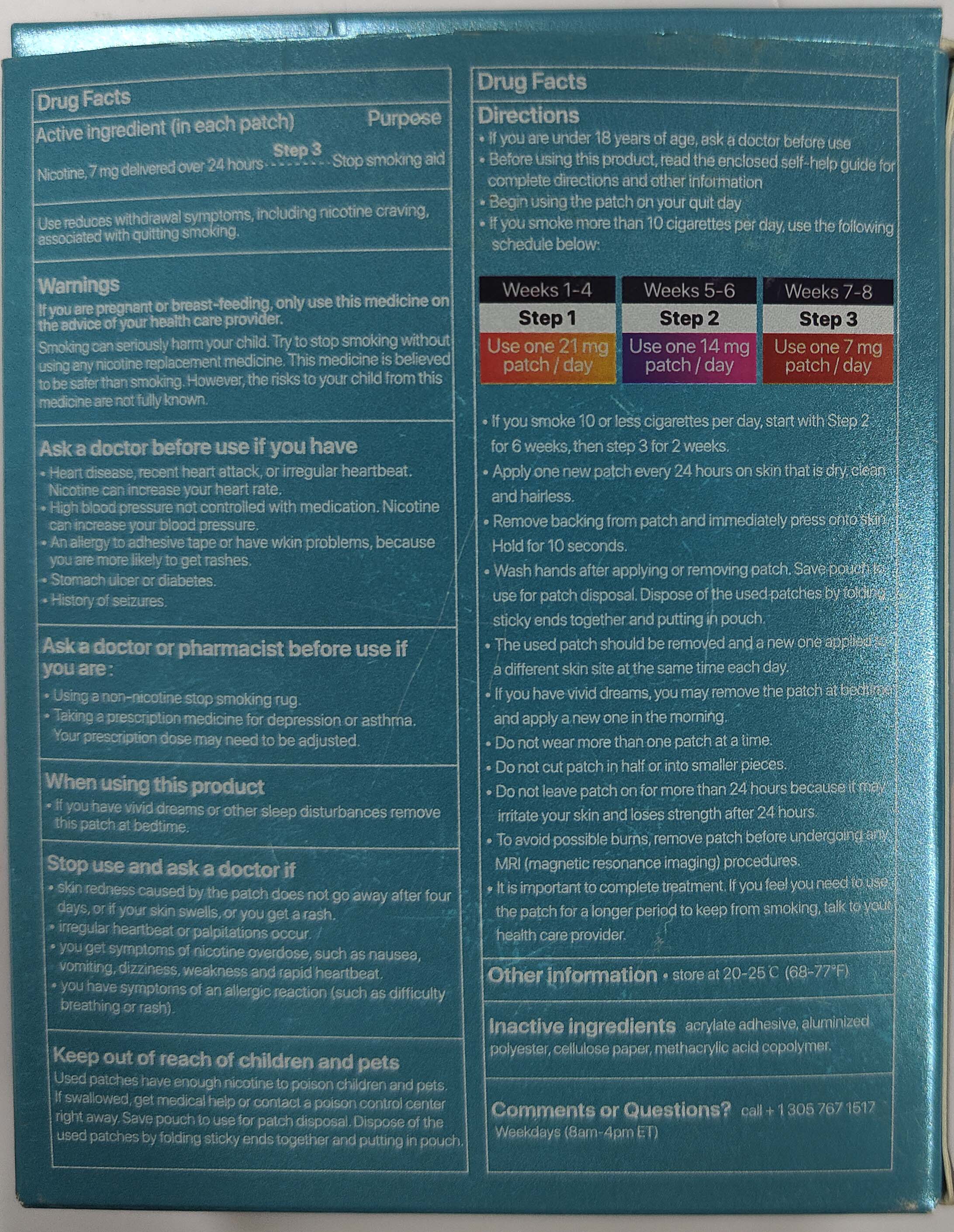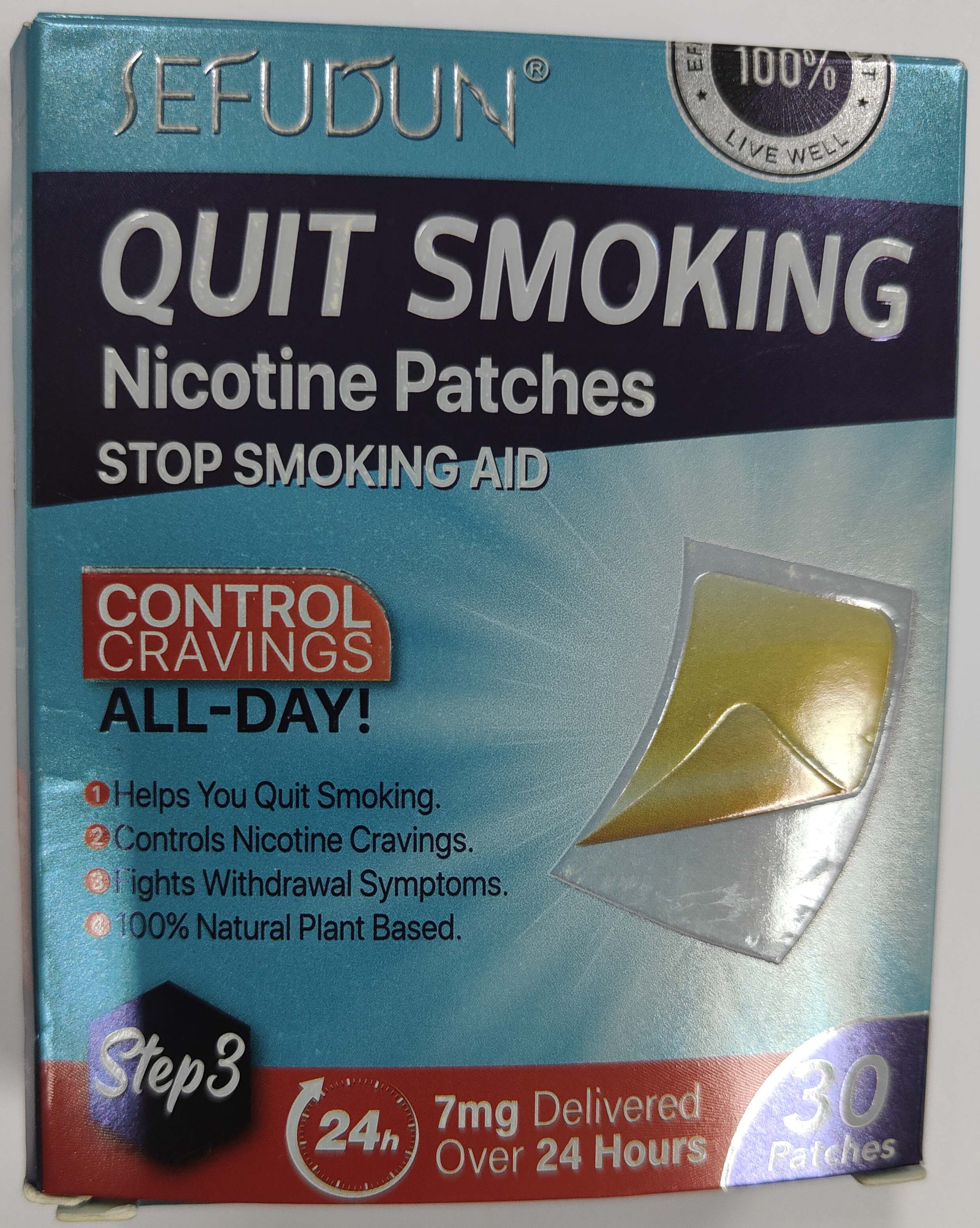 DRUG LABEL: SEFUDUN QUIT SMOKING NICOTINE PATCHES
NDC: 83804-107 | Form: PATCH
Manufacturer: Shenzhen Shandian Jingling Technology Co., Ltd.
Category: homeopathic | Type: HUMAN OTC DRUG LABEL
Date: 20241122

ACTIVE INGREDIENTS: NICOTINE 7 mg/1 1
INACTIVE INGREDIENTS: ACRYLIC ACID; METHACRYLIC ACID - METHYL METHACRYLATE COPOLYMER (1:1); POLYESTER-5 (TG-38)

SEFUDUN QUIT SMOKING NICOTINE PATCHES

ACTIVE INGREDIENT

nicotine

PURPOSE

Stop smoking aid

KEEP OUT OF REACH OF CHILDREN

Used patches have enough nicotine to poison children and petsif swallowed, get medical help or conlact a poison control centerfight away, Save pouch to use for patch disposal. Dispose af theused patches by folding sticky ends together and putting in pouch,

INDICATIONS AND USAGE

Use reduices withdrawal symploms, including nicotine cravingassociated with guitting smokind

WARNINGS

if you are precnant or breast.feeding, only use this medicine onthe advice of your heaith care provider.Smoking can seribusly harm your child. Try to stop smoking withoutusing anvnicotine replacement medicine, This medicine is believedto be safer than smoking. However, the risks to your child from thismedicine are not fully known

DOSAGE AND ADMINISTRATION

if you are under 18 years of age, ask a doctor before use. Before usino this product, read the enclosed self-help guide forcomplete directions and other infolmation.
Begin usio the patch on your quit day.
if you smoke more than 10 cigarettes per day, use the foilowingschedule below:
Weeks 1-4
Step 1
Use one 21 mgpatch / day
Weeks 5-6
Step 2
Use one 14 mgpatch / day
Weeks 7-8
Step 3
Use one 7 mgpatch day

INACTIVE INGREDIENT

methacrylic acid copolymer
POLYESTER-5 (TG-38)
ACRYLIC ACID